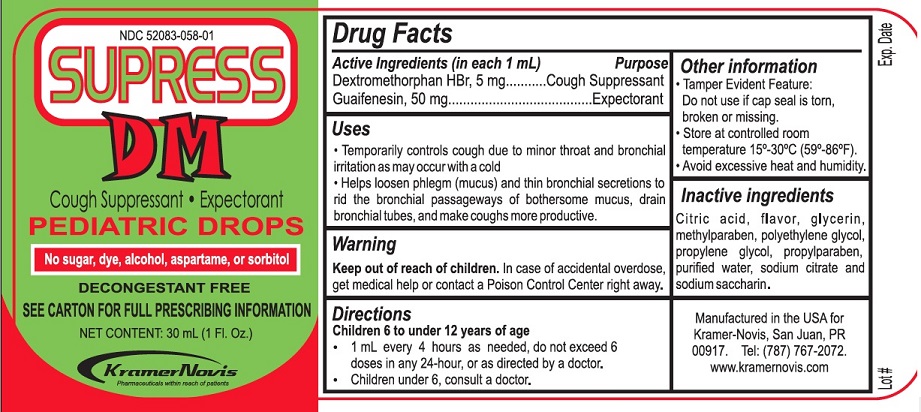 DRUG LABEL: Supress DM
NDC: 52083-058 | Form: SYRUP
Manufacturer: KRAMER NOVIS
Category: otc | Type: HUMAN OTC DRUG LABEL
Date: 20251114

ACTIVE INGREDIENTS: GUAIFENESIN 50 mg/1 mL; DEXTROMETHORPHAN HYDROBROMIDE 5 mg/1 mL
INACTIVE INGREDIENTS: CITRIC ACID MONOHYDRATE; GLYCERIN; METHYLPARABEN; POLYETHYLENE GLYCOL, UNSPECIFIED; PROPYLENE GLYCOL; PROPYLPARABEN; WATER; SODIUM CITRATE, UNSPECIFIED FORM; SACCHARIN SODIUM

Supress DM

Active Ingredients (in each 1 ml)

Dextromethorphan HBr, 5 mg

Guaifenesin, 50 mg

Purpose

Cough Suppressant

Expectorant

Uses

• Temporarily controls cough due to minor throat and bronchial irritation as may occur with a cold
• Helps loosen phlegm (mucus) and thin bronchial secretions to rid the bronchial passageways of bothersome mucus, drain bronchial tubes, and make coughs more productive.

Warnings

Do not use:

in a child who is taking a prescription monoamine oxidase inhibitor (MAOI) (certain drugs for depression, psychiatric, or emotional conditions, or Parkinson's disease) or for 2 weeks after stopping the MAOI drug. If you do not know if your child's prescription drug contains an MAOI, ask a doctor or pharmacist before taking this product.

Ask a doctor before use if your child has

- cough that occurs with too much phlegm (mucus)
- cough that lasts or is chronic such as occurs with asthma.

When using this product do not exceed the recommended dosage.

Stop use and ask a doctor if

- new symptoms occur
- coughs persists for more than 1 week, tends to recur, or is accompanied by fever, rash or persistent headache. These could be signs of a serious condition.

If pregnant or breast-feeding, ask a health professional before use.

Keep out of reach of children. In case of accidental overdose, get medical help or contact a Poison Control Center right away.

Directions

Children 6 to under 12 years of age

• 1 mL every 4 hours as needed, do not exceed 6 doses in any 24-hour, or as directed by a doctor

• Children under 6, consult a doctor

Inactive ingredients

Citric acid, flavor, glycerin, methylparaben, polyethylene glycol, propylene glycol, propylparaben, purified water, sodium citrate and sodium saccharin.

Other information

• Tamper Evident Feature: Do not use if cap seal is torn, broken or missing.

• Store at controlled room temperature 15°-30°C (59°-86°F).

• Avoid excessive heat and humidity.

COUGH SUPPRESSANT

EXPECTORANT

No sugar, dye, alcohol, aspartame or sorbitol

DECONGESTANT FREE

Manufacture in the USA for Kramer-Novis, San Juan, PR 00917. Tel: (787) 767-2072

www.kramernovis.com